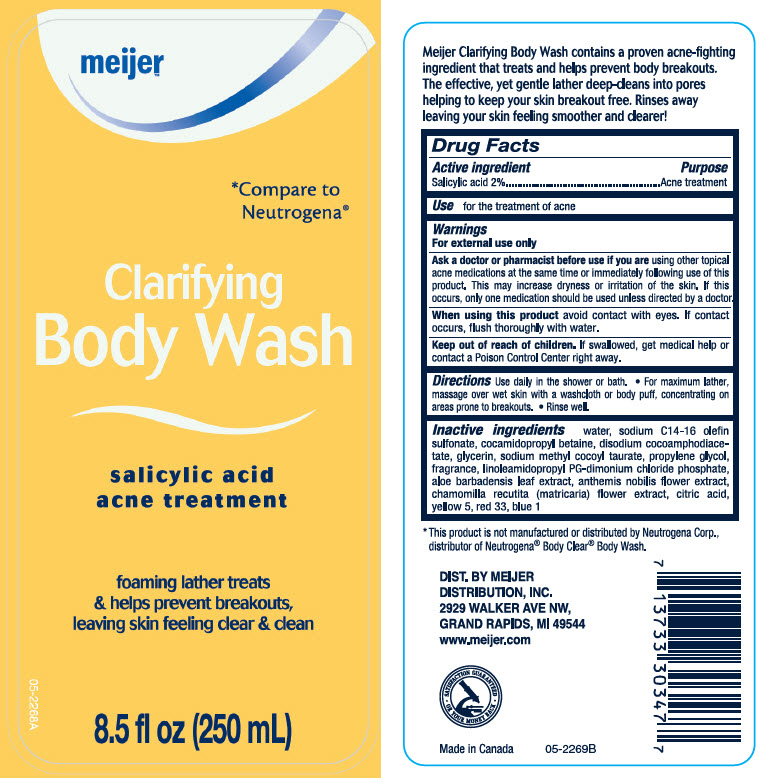 DRUG LABEL: Meijer Clarifying Body Wash
NDC: 41250-627 | Form: LOTION
Manufacturer: Meijer Distribution, Inc
Category: otc | Type: HUMAN OTC DRUG LABEL
Date: 20241107

ACTIVE INGREDIENTS: Salicylic Acid 20 mg/1 mL
INACTIVE INGREDIENTS: Water; Sodium C14-16 Olefin Sulfonate; Cocamidopropyl Betaine; Disodium Cocoamphodiacetate; Glycerin; Sodium Methyl Cocoyl Taurate; Propylene Glycol; LINOLEAMIDOPROPYL PROPYLENE GLYCOL-DIMONIUM CHLORIDE PHOSPHATE; ALOE VERA LEAF; CHAMAEMELUM NOBILE FLOWER; CHAMOMILE; CITRIC ACID MONOHYDRATE; FD&C YELLOW NO. 5; D&C RED NO. 33; FD&C BLUE NO. 1

Meijer™ Clarifying Body Wash
Acne Treatment

Drug Facts

Active ingredients

Salicylic Acid 2.0%

Purpose

Acne Treatment

Use

for the treatment of acne

Warnings

For external use only

Ask a doctor or pharmacist before use if you are using other topical acne medications at the same time or immediately following use of this product. This may increase dryness or irritation of the skin. If this occurs, only one medication should be used unless directed by a doctor.

When using this product avoid contact with eyes. If contact occurs, flush thoroughly with water.

Keep out of reach of children. If swallowed, get medical help or contact a Poison Control Center right away.

Directions

Use daily in the shower or bath

- For maximum lather, massage over wet skin with a washcloth or body puff, concentrating on areas prone to breakouts
- Rinse well.

Inactive ingredients

Water, Sodium C14-16 Olefin Sulfonate, Cocamidopropyl Betaine, Disodium Cocoamphodiacetate, Glycerin, Sodium Methyl Cocoyl Taurate, Propylene Glycol, Fragrance, Linoleamidopropyl PG-Dimonium Chloride Phosphate, Aloe Barbadensis Leaf Extract, Anthemis Nobilis Flower Extract, Chamomilla Recutita (Matricaria) Flower Extract, Citric Acid, Yellow 5, Red 33, Blue 1

DIST. BY MEIJER
DISTRIBUTION, INC.
2929 WALKER AVE NW,
GRAND RAPIDS, MI 49544

PRINCIPAL DISPLAY PANEL - 250 mL Bottle Label

meijer™

*Compare to
Neutrogena®

Clarifying
Body Wash

salicylic acid
acne treatment

foaming lather treats
& helps prevent breakouts,
leaving skin feeling clear & clean

8.5 fl oz (250 mL)

05-2268A